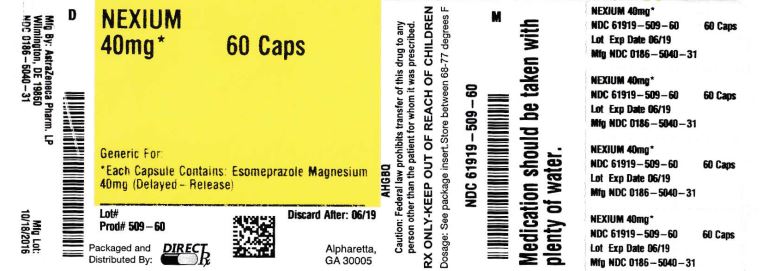 DRUG LABEL: NEXIUM
NDC: 61919-509 | Form: CAPSULE, DELAYED RELEASE
Manufacturer: DIRECT RX
Category: prescription | Type: HUMAN PRESCRIPTION DRUG LABEL
Date: 20190328

ACTIVE INGREDIENTS: ESOMEPRAZOLE MAGNESIUM 40 mg/1 1
INACTIVE INGREDIENTS: GLYCERYL MONOSTEARATE; HYDROXYPROPYL CELLULOSE (1600000 WAMW); HYPROMELLOSES; MAGNESIUM STEARATE; METHACRYLIC ACID; POTASSIUM SORBATE; TALC; TRIETHYL CITRATE; WATER; ANHYDROUS DEXTROSE; POVIDONE, UNSPECIFIED; ANHYDROUS CITRIC ACID; FERRIC OXIDE YELLOW; ALCOHOL

NEXIUM

INDICATIONS & USAGE SECTION

1.1 Treatment of Gastroesophageal Reflux Disease (GERD)

Healing of Erosive Esophagitis

NEXIUM is indicated for the short-term treatment (4 to 8 weeks) in the healing and symptomatic resolution of diagnostically confirmed erosive esophagitis. For those patients who have not healed after 4 to 8 weeks of treatment, an additional 4 to 8 week course of NEXIUM may be considered.

In infants 1 month to less than 1 year, NEXIUM is indicated for short-term treatment (up to 6 weeks) of erosive esophagitis due to acid-mediated GERD.

Maintenance of Healing of Erosive Esophagitis

NEXIUM is indicated to maintain symptom resolution and healing of erosive esophagitis. Controlled studies do not extend beyond 6 months.

Symptomatic Gastroesophageal Reflux Disease

NEXIUM is indicated for short-term treatment (4 to 8 weeks) of heartburn and other symptoms associated with GERD in adults and children 1 year or older.

1.2 Risk Reduction of NSAID-Associated Gastric Ulcer

NEXIUM is indicated for the reduction in the occurrence of gastric ulcers associated with continuous NSAID therapy in patients at risk for developing gastric ulcers. Patients are considered to be at risk due to their age (≥ 60) and/or documented history of gastric ulcers. Controlled studies do not extend beyond 6 months.

1.3 H. pylori Eradication to Reduce the Risk of Duodenal Ulcer Recurrence

Triple Therapy (NEXIUM plus amoxicillin and clarithromycin): NEXIUM, in combination with amoxicillin and clarithromycin, is indicated for the treatment of patients with H. pylori infection and duodenal ulcer disease (active or history of within the past 5 years) to eradicate H. pylori. Eradication of H. pylori has been shown to reduce the risk of duodenal ulcer recurrence [see Dosage and Administration (2)and Clinical Studies (14)].

In patients who fail therapy, susceptibility testing should be done. If resistance to clarithromycin is demonstrated or susceptibility testing is not possible, alternative antimicrobial therapy should be instituted [see Clinical Pharmacology (12.4) and the prescribing information for clarithromycin].

1.4 Pathological Hypersecretory Conditions Including Zollinger-Ellison Syndrome

NEXIUM is indicated for the long-term treatment of pathological hypersecretory conditions, including Zollinger-Ellison Syndrome.

DOSAGE & ADMINISTRATION SECTION

NEXIUM is supplied as delayed-release capsules for oral administration or in packets for preparation of delayed-release oral suspensions. The recommended dosages are outlined in Table 1. NEXIUM should be taken at least one hour before meals.

The duration of proton pump inhibitor administration should be based on available safety and efficacy data specific to the defined indication and dosing frequency, as described in the prescribing information, and individual patient medical needs. Proton pump inhibitor treatment should only be initiated and continued if the benefits outweigh the risks of treatment.

Table 1: Recommended Dosage Schedule of NEXIUM
Indication | Dose | Frequency
Gastroesophageal Reflux Disease (GERD)
Healing of Erosive Esophagitis | 20 mg or 40 mg | Once Daily for 4 to 8 Weeks *
Maintenance of Healing of Erosive Esophagitis | 20 mg | Once Daily †
Symptomatic Gastroesophageal Reflux Disease | 20 mg | Once Daily for 4 Weeks ‡
Pediatric GERD
12 to 17 Year Olds
Healing of Erosive Esophagitis; Symptomatic GERD | 20 mg or 40 mg; 20 mg | Once Daily for 4 to 8 Weeks; Once Daily for 4 Weeks
1 to 11 Year Olds §
Short-term Treatment of Symptomatic GERD | 10 mg | Once Daily for up to 8 Weeks
Healing of Erosive Esophagitis
weight < 20 kg | 10 mg | Once Daily for 8 Weeks
weight ≥ 20 kg | 10 mg or 20 mg | Once Daily for 8 Weeks
1 month to < 1 year old ¶
Erosive esophagitis due to acid-mediated GERD
weight 3 kg to 5 kg | 2.5 mg | Once Daily for up to 6 Weeks
weight > 5 kg to 7.5 kg | 5 mg | Once Daily for up to 6 Weeks
weight >7.5 kg to 12 kg | 10 mg | Once Daily for up to 6 Weeks
Risk Reduction of NSAID-Associated Gastric Ulcer | 20 mg or 40 mg | Once Daily for up to 6 months †
H. pylori Eradication to Reduce the Risk of Duodenal Ulcer Recurrence
Triple Therapy:
NEXIUM | 40 mg | Once Daily for 10 Days
Amoxicillin | 1000 mg | Twice Daily for 10 Days
Clarithromycin | 500 mg | Twice Daily for 10 Days
Pathological Hypersecretory Conditions Including Zollinger-Ellison Syndrome | 40 mg # | ÞTwice Daily
*[See Clinical Studies (14.1) ]The majority of patients are healed within 4 to 8 weeks. For patients who do not heal after 4 to 8 weeks, an additional 4 to 8 weeks of treatment may be considered. †Controlled studies did not extend beyond six months. ‡If symptoms do not resolve completely after 4 weeks, an additional 4 weeks of treatment may be considered. §Doses over 1 mg/kg/day have not been studied. ¶Doses over 1.33 mg/kg/day have not been studied. #The dosage of NEXIUM in patients with pathological hypersecretory conditions varies with the individual patient. Dosage regimens should be adjusted to individual patient needs. ÞDoses up to 240 mg daily have been administered [see Drug Interactions (7)].

Please refer to amoxicillin and clarithromycin prescribing information for Contraindications, Warnings, and dosing in elderly and renally-impaired patients.

Special Populations

Hepatic Insufficiency

In patients with mild to moderate liver impairment (Child Pugh Classes A and B), no dosage adjustment is necessary. For patients with severe liver impairment (Child Pugh Class C), a dose of 20 mg of NEXIUM should not be exceeded [see Clinical Pharmacology (12.3)].

Directions for use specific to the route and available methods of administration for each of these dosage forms are presented in Table 2.

Table 2: Administration Options

Administration Options
(See text following table for additional instructions.)
Dosage Form | Route | Options
Delayed-Release Capsules | Oral | Capsule can be swallowed whole.; -or-; Capsule can be opened and mixed with applesauce.
Delayed-Release Capsules | Nasogastric Tube | Capsule can be opened and the intact granules emptied into a syringe and delivered through the nasogastric tube.
For Delayed-Release Oral Suspension | Oral | For the 2.5 mg and 5 mg strengths, mix the contents of packet with 5 mL of water, leave 2 to 3 minutes to thicken, stir and drink within 30 minutes.; For the 10 mg, 20 mg and 40 mg strengths, mix contents of packet with 15 mL of water, and follow the instructions above.
For Delayed-Release Oral Suspension | Nasogastric or Gastric Tube | For the 2.5 mg and 5 mg strengths, add 5 mL of water to a syringe and then add contents of packet. Shake the syringe; leave 2 to 3 minutes to thicken. Shake the syringe and inject through the nasogastric or gastric tube within 30 minutes.; For the 10 mg, 20 mg and 40 mg strengths, add 15 mL of water, and follow the instructions above.

NEXIUM Delayed-Release Capsules

NEXIUM Delayed-Release Capsules should be swallowed whole.

Alternatively, for patients who have difficulty swallowing capsules, one tablespoon of applesauce can be added to an empty bowl and the NEXIUM Delayed-Release Capsule can be opened, and the granules inside the capsule carefully emptied onto the applesauce. The granules should be mixed with the applesauce and then swallowed immediately: do not store for future use. The applesauce used should not be hot and should be soft enough to be swallowed without chewing. The granules should not be chewed or crushed. If the granules/applesauce mixture is not used in its entirety, the remaining mixture should be discarded immediately.

For patients who have a nasogastric tube in place, NEXIUM Delayed-Release Capsules can be opened and the intact granules emptied into a 60 mL catheter tipped syringe and mixed with 50 mL of water. It is important to only use a catheter tipped syringe when administering NEXIUM through a nasogastric tube. Replace the plunger and shake the syringe vigorously for 15 seconds. Hold the syringe with the tip up and check for granules remaining in the tip. Attach the syringe to a nasogastric tube and deliver the contents of the syringe through the nasogastric tube into the stomach. After administering the granules, the nasogastric tube should be flushed with additional water. Do not administer the granules if they have dissolved or disintegrated.

The mixture must be used immediately after preparation.

NEXIUM For Delayed-Release Oral Suspension

NEXIUM For Delayed-Release Oral Suspension should be administered as follows:

•Empty the contents of a 2.5 mg or 5 mg packet into a container containing 5 mL of water. For the 10 mg, 20 mg, and 40 mg strengths, the contents of a packet should be emptied into a container containing 15 mL of water.•Stir.•Leave 2 to 3 minutes to thicken.•Stir and drink within 30 minutes.•If any medicine remains after drinking, add more water, stir, and drink immediately.•In cases where there is a need to use two packets, they may be mixed in a similar way by adding twice the required amount of water or follow the mixing instructions provided by your pharmacist or doctor.

For patients who have a nasogastric or gastric tube in place, NEXIUM For Delayed-Release Oral Suspension can be administered as follows:

•Add 5 mL of water to a catheter tipped syringe and then add the contents of a 2.5 mg or 5 mg NEXIUM packet. For the 10 mg, 20 mg, and 40 mg strengths, the volume of water in the syringe should be 15 mL. It is important to only use a catheter tipped syringe when administering NEXIUM through a nasogastric tube or gastric tube.•Immediately shake the syringe and leave 2 to 3 minutes to thicken.•Shake the syringe and inject through the nasogastric or gastric tube, French size 6 or larger, into the stomach within 30 minutes.•Refill the syringe with an equal amount of water (5 mL or 15 mL).•Shake and flush any remaining contents from the nasogastric or gastric tube into the stomach.

DOSAGE FORMS & STRENGTHS SECTION

NEXIUM Delayed-Release Capsules, 20 mg - opaque, hard gelatin, amethyst colored capsules with two radial bars in yellow on the cap and NEXIUM 20 mg in yellow on the body.

NEXIUM Delayed-Release Capsules, 40 mg - opaque, hard gelatin, amethyst colored capsules with three radial bars in yellow on the cap and NEXIUM 40 mg in yellow on the body.

NEXIUM For Delayed-Release Oral Suspension, 2.5 mg, 5 mg, 10 mg, 20 mg or 40 mg - unit dose packet containing a fine yellow powder, consisting of white to pale brownish esomeprazole granules and pale yellow inactive granules.

CONTRAINDICATIONS SECTION

NEXIUM is contraindicated in patients with known hypersensitivity to proton pump inhibitors. Hypersensitivity reactions, e.g., angioedema and anaphylactic shock, have been reported with NEXIUM use.

For information about contraindications of antibacterial agents (clarithromycin and amoxicillin) indicated in combination with NEXIUM, refer to the CONTRAINDICATIONS section of their package inserts.

WARNINGS AND PRECAUTIONS SECTION

5.1 Concurrent Gastric Malignancy

Symptomatic response to therapy with NEXIUM does not preclude the presence of gastric malignancy.

5.2 Atrophic Gastritis

Atrophic gastritis has been noted occasionally in gastric corpus biopsies from patients treated long-term with omeprazole, of which esomeprazole is an enantiomer.

5.3 Clostridium difficile associated diarrhea

Published observational studies suggest that PPI therapy like NEXIUM may be associated with an increased risk of Clostridiumdifficile associated diarrhea, especially in hospitalized patients. This diagnosis should be considered for diarrhea that does not improve [see Adverse Reactions (6.2)].

Patients should use the lowest dose and shortest duration of PPI therapy appropriate to the condition being treated.

Clostridium diffficile associated diarrhea (CDAD) has been reported with use of nearly all antibacterial agents. For more information specific to antibacterial agents (clarithromycin and amoxicillin) indicated for use in combination with NEXIUM, refer to WARNINGS and PRECAUTIONS sections of those package inserts.

5.4 Interaction with Clopidogrel

Avoid concomitant use of NEXIUM with clopidogrel. Clopidogrel is a prodrug. Inhibition of platelet aggregation by clopidogrel is entirely due to an active metabolite. The metabolism of clopidogrel to its active metabolite can be impaired by use with concomitant medications, such as esomeprazole, that inhibit CYP2C19 activity. Concomitant use of clopidogrel with 40 mg esomeprazole reduces the pharmacological activity of clopidogrel. When using NEXIUM consider alternative anti-platelet therapy [see Drug Interactions (7.3) and Pharmacokinetics (12.3)].

5.5 Bone Fracture

Several published observational studies suggest that proton pump inhibitor (PPI) therapy may be associated with an increased risk for osteoporosis-related fractures of the hip, wrist, or spine. The risk of fracture was increased in patients who received high-dose, defined as multiple daily doses, and long-term PPI therapy (a year or longer). Patients should use the lowest dose and shortest duration of PPI therapy appropriate to the condition being treated. Patients at risk for osteoporosis-related fractures should be managed according to established treatment guidelines [see Dosage and Administration (2) and Adverse Reactions (6.2)].

5.6 Hypomagnesemia

Hypomagnesemia, symptomatic and asymptomatic, has been reported rarely in patients treated with PPIs for at least three months, in most cases after a year of therapy. Serious adverse events include tetany, arrhythmias, and seizures. In most patients, treatment of hypomagnesemia required magnesium replacement and discontinuation of the PPI.

For patients expected to be on prolonged treatment or who take PPIs with medications such as digoxin or drugs that may cause hypomagnesemia (e.g., diuretics), health care professionals may consider monitoring magnesium levels prior to initiation of PPI treatment and periodically [see Adverse Reactions (6.2)].

5.7 Concomitant use of NEXIUM with St. John’s Wort or Rifampin

Drugs which induce CYP2C19 or CYP3A4 (such as St. John’s Wort or rifampin) can substantially decrease esomeprazole concentrations [see Drug Interactions (7.3)]. Avoid concomitant use of NEXIUM with St. John’s Wort or rifampin.

5.8 Interactions with Diagnostic Investigations for Neuroendocrine Tumors

Serum chromogranin A (CgA) levels increase secondary to drug-induced decreases in gastric acidity. The increased CgA level may cause false positive results in diagnostic investigations for neuroendocrine tumors. Healthcare providers should temporarily stop esomeprazole treatment at least 14 days before assessing CgA levels and consider repeating the test if initial CgA levels are high. If serial tests are performed (e.g. for monitoring), the same commercial laboratory should be used for testing, as reference ranges between tests may vary [see Clinical Pharmacology (12.2)].

5.9 Concomitant use of NEXIUM with Methotrexate

Literature suggests that concomitant use of PPIs with methotrexate (primarily at high dose; see methotrexate prescribing information) may elevate and prolong serum levels of methotrexate and/or its metabolite, possibly leading to methotrexate toxicities. In high-dose methotrexate administration a temporary withdrawal of the PPI may be considered in some patients [see Drug Interactions (7.7)].

ADVERSE REACTIONS SECTION

6.1 Clinical Trials Experience

Because clinical trials are conducted under widely varying conditions, adverse reaction rates observed in the clinical trials of a drug cannot be directly compared to rates in the clinical trials of another drug and may not reflect the rates observed in practice.

Adults

The safety of NEXIUM was evaluated in over 15,000 patients (aged 18 to 84 years) in clinical trials worldwide including over 8,500 patients in the United States and over 6,500 patients in Europe and Canada. Over 2,900 patients were treated in long-term studies for up to 6-12 months. In general, NEXIUM was well tolerated in both short and long-term clinical trials.

The safety in the treatment of healing of erosive esophagitis was assessed in four randomized comparative clinical trials, which included 1,240 patients on NEXIUM 20 mg, 2,434 patients on NEXIUM 40 mg, and 3,008 patients on omeprazole 20 mg daily. The most frequently occurring adverse reactions (≥1%) in all three groups were headache (5.5, 5, and 3.8, respectively) and diarrhea (no difference among the three groups). Nausea, flatulence, abdominal pain, constipation, and dry mouth occurred at similar rates among patients taking NEXIUM or omeprazole.

Additional adverse reactions that were reported as possibly or probably related to NEXIUM with an incidence < 1% are listed below by body system:

Body as a Whole: abdomen enlarged, allergic reaction, asthenia, back pain, chest pain, substernal chest pain, facial edema, peripheral edema, hot flushes, fatigue, fever, flu-like disorder, generalized edema, leg edema, malaise, pain, rigors;

Cardiovascular: flushing, hypertension, tachycardia;

Endocrine: goiter;

Gastrointestinal: bowel irregularity, constipation aggravated, dyspepsia, dysphagia, dysplasia GI, epigastric pain, eructation, esophageal disorder, frequent stools, gastroenteritis, GI hemorrhage, GI symptoms not otherwise specified, hiccup, melena, mouth disorder, pharynx disorder, rectal disorder, serum gastrin increased, tongue disorder, tongue edema, ulcerative stomatitis, vomiting;

Hearing: earache, tinnitus;

Hematologic: anemia, anemia hypochromic, cervical lymphadenopathy, epistaxis, leukocytosis, leukopenia, thrombocytopenia;

Hepatic: bilirubinemia, hepatic function abnormal, SGOT increased, SGPT increased;

Metabolic/Nutritional: glycosuria, hyperuricemia, hyponatremia, increased alkaline phosphatase, thirst, vitamin B12 deficiency, weight increase, weight decrease;

Musculoskeletal: arthralgia, arthritis aggravated, arthropathy, cramps, fibromyalgia syndrome, hernia, polymyalgia rheumatica;

Nervous System/Psychiatric: anorexia, apathy, appetite increased, confusion, depression aggravated, dizziness, hypertonia, nervousness, hypoesthesia, impotence, insomnia, migraine, migraine aggravated, paresthesia, sleep disorder, somnolence, tremor, vertigo, visual field defect;

Reproductive: dysmenorrhea, menstrual disorder, vaginitis;

Respiratory: asthma aggravated, coughing, dyspnea, larynx edema, pharyngitis, rhinitis, sinusitis;

Skin and Appendages: acne, angioedema, dermatitis, pruritus, pruritus ani, rash, rash erythematous, rash maculo-papular, skin inflammation, sweating increased, urticaria;

Special Senses: otitis media, parosmia, taste loss, taste perversion;

Urogenital: abnormal urine, albuminuria, cystitis, dysuria, fungal infection, hematuria, micturition frequency, moniliasis, genital moniliasis, polyuria;

Visual: conjunctivitis, vision abnormal.

The following potentially clinically significant laboratory changes in clinical trials, irrespective of relationship to NEXIUM, were reported in ≤ 1% of patients: increased creatinine, uric acid, total bilirubin, alkaline phosphatase, ALT, AST, hemoglobin, white blood cell count, platelets, serum gastrin, potassium, sodium, thyroxine and thyroid stimulating hormone [see Clinical Pharmacology (12)]. Decreases were seen in hemoglobin, white blood cell count, platelets, potassium, sodium, and thyroxine.

Endoscopic findings that were reported as adverse reactions include: duodenitis, esophagitis, esophageal stricture, esophageal ulceration, esophageal varices, gastric ulcer, gastritis, hernia, benign polyps or nodules, Barrett’s esophagus, and mucosal discoloration.

The incidence of treatment-related adverse reactions during 6-month maintenance treatment was similar to placebo. There were no differences in types of related adverse reactions seen during maintenance treatment up to 12 months compared to short-term treatment.

Two placebo-controlled studies were conducted in 710 patients for the treatment of symptomatic gastroesophageal reflux disease. The most common adverse reactions that were reported as possibly or probably related to NEXIUM were diarrhea (4.3%), headache (3.8%), and abdominal pain (3.8%).

Pediatrics

The safety of NEXIUM was evaluated in 316 pediatric and adolescent patients aged 1 to 17 years in four clinical trials for the treatment of symptomatic GERD [see Clinical Studies (14.2)]. In 109 pediatric patients aged 1 to 11 years, the most frequently reported (at least 1%) treatment-related adverse reactions in these patients were diarrhea (2.8%), headache (1.9%) and somnolence (1.9%). In 149 pediatric patients aged 12 to 17 years the most frequently reported (at least 2%) treatment-related adverse reactions in these patients were headache (8.1%), abdominal pain (2.7%), diarrhea (2%), and nausea (2%).

The safety of NEXIUM was evaluated in 167 pediatric patients from birth to <1 year of age in three clinical trials [see Clinical Studies (14.3)]. In a study that included 26 pediatric patients aged birth to 1 month there were no treatment related adverse reactions. In a study that included 43 pediatric patients age 1 to 11 months, inclusive the most frequently reported (at least 5%) adverse reactions, irrespective of causality, were irritability and vomiting. In a study that included 98 pediatric patients, age 1 to 11 months, inclusive exposed to esomeprazole for up to 6 weeks (including 39 patients randomized to the withdrawal phase), there were 4 treatment-related adverse reactions: abdominal pain (1%), regurgitation (1%), tachypnea (1%), and increased ALT (1%).

No new safety concerns were identified in pediatric patients.

Combination Treatment with Amoxicillin and Clarithromycin

In clinical trials using combination therapy with NEXIUM plus amoxicillin and clarithromycin, no additional adverse reactions specific to these drug combinations were observed. Adverse reactions that occurred were limited to those observed when using NEXIUM, amoxicillin, or clarithromycin alone.

The most frequently reported drug-related adverse reactions for patients who received triple therapy for 10 days were diarrhea (9.2%), taste perversion (6.6%), and abdominal pain (3.7%). No treatment-emergent adverse reactions were observed at higher rates with triple therapy than were observed with NEXIUM alone.

For more information on adverse reactions with amoxicillin or clarithromycin, refer to their package inserts, Adverse Reactions sections.

In clinical trials using combination therapy with NEXIUM plus amoxicillin and clarithromycin, no additional increased laboratory abnormalities particular to these drug combinations were observed.

For more information on laboratory changes with amoxicillin or clarithromycin, refer to their package inserts, Adverse Reactions section.

6.2 Postmarketing Experience

The following adverse reactions have been identified during post-approval use of NEXIUM. Because these reactions are reported voluntarily from a population of uncertain size, it is not always possible to reliably estimate their frequency or establish a causal relationship to drug exposure. These reports are listed below by body system:

Blood And Lymphatic: agranulocytosis, pancytopenia;

Eye: blurred vision;

Gastrointestinal: pancreatitis; stomatitis; microscopic colitis

Hepatobiliary: hepatic failure, hepatitis with or without jaundice;

Immune System: anaphylactic reaction/shock;

Infections and Infestations: GI candidiasis; Clostridium difficile associated diarrhea;

Metabolism and nutritional disorders: hypomagnesemia, with or without hypocalcemia and/or hypokalemia

Musculoskeletal and Connective Tissue: muscular weakness, myalgia, bone fracture;

Nervous System: hepatic encephalopathy, taste disturbance;

Psychiatric: aggression, agitation, depression, hallucination;

Renal and Urinary: interstitial nephritis;

Reproductive System and Breast: gynecomastia;

Respiratory, Thoracic, and Mediastinal: bronchospasm;

Skin and Subcutaneous Tissue: alopecia, erythema multiforme, hyperhidrosis, photosensitivity, Stevens-Johnson syndrome, toxic epidermal necrolysis (some fatal).

DRUG INTERACTIONS SECTION

7.1 Interference with Antiretroviral Therapy

Concomitant use of atazanavir and nelfinavir with proton pump inhibitors is not recommended. Co-administration of atazanavir with proton pump inhibitors is expected to substantially decrease atazanavir plasma concentrations and may result in a loss of therapeutic effect and the development of drug resistance. Co-administration of saquinavir with proton pump inhibitors is expected to increase saquinavir concentrations, which may increase toxicity and require dose reduction.

Omeprazole, of which esomeprazole is an enantiomer, has been reported to interact with some antiretroviral drugs. The clinical importance and the mechanisms behind these interactions are not always known. Increased gastric pH during omeprazole treatment may change the absorption of the antiretroviral drug. Other possible interaction mechanisms are via CYP2C19.

Reduced concentrations of atazanavir and nelfinavir

For some antiretroviral drugs, such as atazanavir and nelfinavir, decreased serum levels have been reported when given together with omeprazole. Following multiple doses of nelfinavir (1250 mg, twice daily) and omeprazole (40 mg daily), AUC was decreased by 36% and 92%, Cmax by 37% and 89% and Cmin by 39% and 75% respectively for nelfinavir and M8. Following multiple doses of atazanavir (400 mg, daily) and omeprazole (40 mg, daily, 2 hr before atazanavir), AUC was decreased by 94%, Cmax by 96%, and Cmin by 95%. Concomitant administration with omeprazole and drugs such as atazanavir and nelfinavir is therefore not recommended.

Increased concentrations of saquinavir

For other antiretroviral drugs, such as saquinavir, elevated serum levels have been reported, with an increase in AUC by 82%, in Cmax by 75%, and in Cmin by 106%, following multiple dosing of saquinavir/ritonavir (1000/100 mg) twice daily for 15 days with omeprazole 40 mg daily co-administered days 11 to 15. Therefore, clinical and laboratory monitoring for saquinavir toxicity is recommended during concurrent use with NEXIUM. Dose reduction of saquinavir should be considered from the safety perspective for individual patients.

There are also some antiretroviral drugs of which unchanged serum levels have been reported when given with omeprazole.

7.2 Drugs for Which Gastric pH Can Affect Bioavailability

Esomeprazole inhibits gastric acid secretion. Therefore, esomeprazole may interfere with the absorption of drugs where gastric pH is an important determinant of bioavailability. Like with other drugs that decrease the intragastric acidity, the absorption of drugs such as ketoconazole, atazanavir, iron salts, and erlotinib can decrease, while the absorption of drugs such as digoxin can increase during treatment with esomeprazole. Concomitant treatment with omeprazole (20 mg daily) and digoxin in healthy subjects increased the bioavailability of digoxin by 10% (30% in two subjects). Esomeprazole is an enantiomer of omeprazole. Co-administration of digoxin with esomeprazole is expected to increase the systemic exposure of digoxin. Therefore, patients may need to be monitored when digoxin is taken concomitantly with esomeprazole.

7.3 Effects on Hepatic Metabolism/Cytochrome P-450 Pathways

Esomeprazole is extensively metabolized in the liver by CYP2C19 and CYP3A4. In vitro and in vivo studies have shown that esomeprazole is not likely to inhibit CYPs 1A2, 2A6, 2C9, 2D6, 2E1, and 3A4. No clinically relevant interactions with drugs metabolized by these CYP enzymes would be expected. Drug interaction studies have shown that esomeprazole does not have any clinically significant interactions with phenytoin, warfarin, quinidine, clarithromycin, or amoxicillin.

However, post-marketing reports of changes in prothrombin measures have been received among patients on concomitant warfarin and esomeprazole therapy. Increases in INR and prothrombin time may lead to abnormal bleeding and even death. Patients treated with proton pump inhibitors and warfarin concomitantly may need to be monitored for increases in INR and prothrombin time.

Esomeprazole may potentially interfere with CYP2C19, the major esomeprazole metabolizing enzyme. Co-administration of esomeprazole 30 mg and diazepam, a CYP2C19 substrate, resulted in a 45% decrease in clearance of diazepam.

Clopidogrel

Clopidogrel is metabolized to its active metabolite in part by CYP2C19. Concomitant use of esomeprazole 40 mg results in reduced plasma concentrations of the active metabolite of clopidogrel and a reduction in platelet inhibition. Avoid concomitant administration of NEXIUM with clopidogrel. When using NEXIUM, consider use of alternative anti-platelet therapy [see Pharmacokinetics (12.3)].

Omeprazole acts as an inhibitor of CYP2C19. Omeprazole, given in doses of 40 mg daily for one week to 20 healthy subjects in cross-over study, increased Cmax and AUC of cilostazol by 18% and 26% respectively. Cmax and AUC of one of its active metabolites, 3,4-dihydrocilostazol, which has 4-7 times the activity of cilostazol, were increased by 29% and 69% respectively. Co-administration of cilostazol with esomeprazole is expected to increase concentrations of cilostazol and its above mentioned active metabolite. Therefore a dose reduction of cilostazol from 100 mg twice daily to 50 mg twice daily should be considered.

Concomitant administration of esomeprazole and a combined inhibitor of CYP2C19 and CYP3A4, such as voriconazole, may result in more than doubling of the esomeprazole exposure. Dose adjustment of esomeprazole is not normally required. However, in patients with Zollinger-Ellison’s Syndrome, who may require higher doses up to 240 mg/day, dose adjustment may be considered.

Drugs known to induce CYP2C19 or CYP3A4 or both (such as rifampin) may lead to decreased esomeprazole serum levels. Omeprazole, of which esomeprazole is an enantiomer, has been reported to interact with St. John’s Wort an inducer of CYP3A4. In a cross-over study in 12 healthy male subjects, St. John’s Wort (300 mg three times daily for 14 days) significantly decreased the systemic exposure of omeprazole in CYP2C19 poor metabolisers (Cmax and AUC decreased by 37.5% and 37.9%, respectively) and extensive metabolisers (Cmax and AUC decreased by 49.6 % and 43.9%, respectively). Avoid concomitant use of St. John’s Wort or rifampin with NEXIUM.

7.4 Interactions With Investigations of Neuroendocrine Tumors

Drug-induced decrease in gastric acidity results in enterochromaffin-like cell hyperplasia and increased Chromogranin A levels which may interfere with investigations for neuroendocrine tumors [see Warnings and Precautions (5.7)and Clinical Pharmacology (12.2)].

7.5 Tacrolimus

Concomitant administration of esomeprazole and tacrolimus may increase the serum levels of tacrolimus.

7.6 Combination Therapy with Clarithromycin

Co-administration of esomeprazole, clarithromycin, and amoxicillin has resulted in increases in the plasma levels of esomeprazole and 14-hydroxyclarithromycin [see Clinical Pharmacology (12.4)].

Concomitant administration of clarithromycin with other drugs can lead to serious adverse reactions due to drug interactions [see Warnings and Precautions in prescribing information for clarithromycin]. Because of these drug interactions, clarithromycin is contraindicated for co-administration with certain drugs [see Contraindications in prescribing information for clarithromycin].

7.7 Methotrexate

Case reports, published population pharmacokinetic studies, and retrospective analyses suggest that concomitant administration of PPIs and methotrexate (primarily at high dose; see methotrexate prescribing information) may elevate and prolong serum levels of methotrexate and/or its metabolite hydroxymethotrexate. However, no formal drug interaction studies of methotrexate with PPIs have been conducted [see Warnings and Precautions (5.8)].

USE IN SPECIFIC POPULATIONS SECTION

8.1 Pregnancy

Pregnancy Category C

Risk Summary

There are no adequate and well-controlled studies with NEXIUM in pregnant women. Esomeprazole is the S-isomer of omeprazole. Available epidemiologic data fail to demonstrate an increased risk of major congenital malformations or other adverse pregnancy outcomes with first trimester omeprazole use.

Teratogenicity was not observed in animal reproduction studies with administration of oral esomeprazole magnesium in rats and rabbits with doses about 57 times and 35 times, respectively, an oral human dose of 40 mg. However, changes in bone morphology were observed in offspring of rats dosed through most of pregnancy and lactation at doses equal to or greater than approximately 33.6 times an oral human dose of 40 mg (see Animal Data). Because of the observed effect at high doses of esomeprazole magnesium on developing bone in rat studies, NEXIUM should be used during pregnancy only if the potential benefit justifies the potential risk to the fetus.

Human Data

Esomeprazole is the S-isomer of omeprazole. Four epidemiological studies compared the frequency of congenital abnormalities among infants born to women who used omeprazole during pregnancy with the frequency of abnormalities among infants of women exposed to H2-receptor antagonists or other controls.

A population-based retrospective cohort epidemiological study from the Swedish Medical Birth Registry, covering approximately 99% of pregnancies, from 1995-99, reported on 955 infants (824 exposed during the first trimester with 39 of these exposed beyond first trimester, and 131 exposed after the first trimester) whose mothers used omeprazole during pregnancy. The number of infants exposed in utero to omeprazole that had any malformation, low birth weight, low Apgar score, or hospitalization was similar to the number observed in this population. The number of infants born with ventricular septal defects and the number of stillborn infants was slightly higher in the omeprazole-exposed infants than the expected number in this population.

A population-based retrospective cohort study covering all live births in Denmark from 1996-2009, reported on 1,800 live births whose mothers used omeprazole during the first trimester of pregnancy and 837, 317 live births whose mothers did not use any proton pump inhibitor. The overall rate of birth defects in infants born to mothers with first trimester exposure to omeprazole was 2.9% and 2.6% in infants born to mothers not exposed to any proton pump inhibitor during the first trimester.

A retrospective cohort study reported on 689 pregnant women exposed to either H2-blockers or omeprazole in the first trimester (134 exposed to omeprazole) and 1,572 pregnant women unexposed to either during the first trimester. The overall malformation rate in offspring born to mothers with first trimester exposure to omeprazole, an H2-blocker, or were unexposed was 3.6%, 5.5%, and 4.1% respectively.

A small prospective observational cohort study followed 113 women exposed to omeprazole during pregnancy (89% first trimester exposures). The reported rate of major congenital malformations was 4% in the omeprazole group, 2% in controls exposed to non-teratogens, and 2.8% in disease paired controls. Rates of spontaneous and elective abortions, preterm deliveries, gestational age at delivery, and mean birth weight were similar among the groups.

Several studies have reported no apparent adverse short-term effects on the infant when single dose oral or intravenous omeprazole was administered to over 200 pregnant women as premedication for cesarean section under general anesthesia.

Animal Data

Reproduction studies have been performed with esomeprazole magnesium in rats at oral doses up to 280 mg/kg/day (about 57 times an oral human dose of 40 mg on a body surface area basis) and in rabbits at oral doses up to 86 mg/kg/day (about 35 times an oral human dose of 40 mg on a body surface area basis) and have revealed no evidence of impaired fertility or harm to the fetus due to esomeprazole magnesium.

A pre- and postnatal developmental toxicity study in rats with additional endpoints to evaluate bone development was performed with esomeprazole magnesium at oral doses of 14 to 280 mg/kg/day (about 3.4 to 57 times an oral human dose of 40 mg on a body surface area basis). Neonatal/early postnatal (birth to weaning) survival was decreased at doses equal to or greater than 138 mg/kg/day (about 33 times an oral human dose of 40 mg on a body surface area basis). Body weight and body weight gain were reduced and neurobehavioral or general developmental delays in the immediate post-weaning timeframe were evident at doses equal to or greater than 69 mg/kg/day (about 16.8 times an oral human dose of 40 mg on a body surface area basis). In addition, decreased femur length, width and thickness of cortical bone, decreased thickness of the tibial growth plate and minimal to mild bone marrow hypocellularity were noted at doses equal to or greater than 14 mg/kg/day (about 3.4 times an oral human dose of 40 mg on a body surface area basis). Physeal dysplasia in the femur was observed in offspring of rats treated with oral doses of esomeprazole magnesium at doses equal to or greater than 138 mg/kg/day (about 33.6 times an oral human dose of 40 mg on a body surface area basis).

Effects on maternal bone were observed in pregnant and lactating rats in a pre- and postnatal toxicity study when esomeprazole magnesium was administered at oral doses of 14 to 280 mg/kg/day (about 3.4 to 57 times an oral human dose of 40 mg on a body surface area basis). When rats were dosed from gestational day 7 through weaning on postnatal day 21, a statistically significant decrease in maternal femur weight of up to 14% (as compared to placebo treatment) was observed at doses equal to or greater than 138 mg/kg/day (about 33.6 times an oral human dose of 40 mg on a body surface area basis).

A pre- and postnatal development study in rats with esomeprazole strontium (using equimolar doses compared to esomeprazole magnesium study) produced similar results in dams and pups as described above.

8.3 Nursing Mothers

Esomeprazole is likely present in human milk. Esomeprazole is the S-isomer of omeprazole and limited data indicate that maternal doses of omeprazole 20 mg daily produce low levels in human milk. Caution should be exercised when Nexium is administered to a nursing woman.

8.4 Pediatric Use

The safety and effectiveness of NEXIUM have been established in pediatric patients 1 to 17 years of age for short-term treatment (up to eight weeks) of GERD. The safety and effectiveness of NEXIUM have been established in pediatric patients 1 month to less than 1 year for short-term treatment (up to 6 weeks) of erosive esophagitis due to acid-mediated GERD. However, the safety and effectiveness of NEXIUM have not been established in patients less than 1 month of age.

1 to 17 years of age

Use of NEXIUM in pediatric and adolescent patients 1 to 17 years of age for short-term treatment (up to eight weeks) of GERD is supported by extrapolation of results from adequate and well-controlled studies for adults and safety and pharmacokinetic studies performed in pediatric and adolescent patients [see Dosage and Administration (2), Adverse Reactions (6.1), Clinical Pharmacology (12.3), and Clinical Studies (14.3)]. The safety and effectiveness of NEXIUM for other pediatric uses have not been established.

Erosive esophagitis due to acid-mediated GERD in infants 1 month to less than one year of age

Use of NEXIUM in pediatric patients 1 month to less than 1 year of age for treatment (up to 6 weeks) of erosive esophagitis due to acid-mediated GERD is supported by extrapolation of results from adequate and well-controlled studies for adults and safety, pharmacokinetic, and pharmacodynamic studies performed in pediatric patients [see Dosage and Administration (2), Adverse Reactions (6.1), Clinical Pharmacology (12.3), and Clinical Studies (14.3)].

Symptomatic GERD in infants 1 month to less than one year of age

There was no statistically significant difference between NEXIUM and placebo in the rate of discontinuation due to symptom worsening in a multicenter, randomized, double-blind, controlled, treatment-withdrawal study of 98 patients ages 1 to 11 months, inclusive. Patients were enrolled if they had either a clinical diagnosis of suspected GERD, symptomatic GERD, or endoscopically proven GERD. Twenty of 98 enrolled patients underwent endoscopy, and 6 patients were found to have erosive esophagitis on endoscopy at baseline. All patients received NEXIUM Delayed-Release Oral Suspension once daily during a two-week, open-label phase of the study.

There were 80 patients who attained a pre-specified level of symptom improvement and who entered the double-blind phase, in which they were randomized in equal proportions to receive NEXIUM or placebo for the next four weeks. Efficacy was assessed by observing the time from randomization to study discontinuation due to symptom worsening during the four-week, treatment-withdrawal phase.

The following pharmacokinetic and pharmacodynamic information was obtained in pediatric patients with GERD aged birth to less than one year of age. In infants (1 to 11 months old, inclusive) given NEXIUM 1 mg/kg once daily, the percent time with intragastric pH > 4 increased from 29% at baseline to 69% on Day 7, which is similar to the pharmacodynamic effect in adults [see Clinical Pharmacology (12.2)]. Apparent clearance (CL/F) increases with age in pediatric patients from birth to 2 years of age.

Neonates 0 to 1 month of age

Following administration of oral NEXIUM in neonates the geometric mean (range) for the apparent clearance (CL/F) was 0.55 L/h/kg (0.25-1.6 L/h/kg).

The safety and effectiveness of NEXIUM in neonates have not been established.

8.5 Geriatric Use

Of the total number of patients who received NEXIUM in clinical trials, 1459 were 65 to 74 years of age and 354 patients were ≥ 75 years of age.

No overall differences in safety and efficacy were observed between the elderly and younger individuals, and other reported clinical experience has not identified differences in responses between the elderly and younger patients, but greater sensitivity of some older individuals cannot be ruled out.

OVERDOSAGE SECTION

A single oral dose of esomeprazole at 510 mg/kg (about 103 times the human dose on a body surface area basis), was lethal to rats. The major signs of acute toxicity were reduced motor activity, changes in respiratory frequency, tremor, ataxia, and intermittent clonic convulsions.

The symptoms described in connection with deliberate NEXIUM overdose (limited experience of doses in excess of 240 mg/day) are transient. Single doses of 80 mg of esomeprazole were uneventful. Reports of overdosage with omeprazole in humans may also be relevant. Doses ranged up to 2,400 mg (120 times the usual recommended clinical dose). Manifestations were variable, but included confusion, drowsiness, blurred vision, tachycardia, nausea, diaphoresis, flushing, headache, dry mouth, and other adverse reactions similar to those seen in normal clinical experience (see omeprazole package insert - Adverse Reactions). No specific antidote for esomeprazole is known. Since esomeprazole is extensively protein bound, it is not expected to be removed by dialysis. In the event of overdosage, treatment should be symptomatic and supportive.

As with the management of any overdose, the possibility of multiple drug ingestion should be considered. For current information on treatment of any drug overdose contact a Poison Control Center at 1–800–222–1222.

DESCRIPTION SECTION

The active ingredient in the proton pump inhibitor NEXIUM® (esomeprazole magnesium) Delayed-Release Capsules for oral administration and NEXIUM (esomeprazole magnesium) For Delayed-Release Oral Suspension is bis(5-methoxy-2-[(S)-[(4-methoxy-3,5-dimethyl-2-pyridinyl)methyl]sulfinyl]-1H-benzimidazole-1-yl) magnesium trihydrate. Esomeprazole is the S-isomer of omeprazole, which is a mixture of the S- and R- isomers. (Initial U.S. approval of esomeprazole magnesium: 2001). Its molecular formula is (C17H18N3O3S)2Mg x 3 H2O with molecular weight of 767.2 as a trihydrate and 713.1 on an anhydrous basis. The structural formula is:

The magnesium salt is a white to slightly colored crystalline powder. It contains 3 moles of water of solvation and is slightly soluble in water. The stability of esomeprazole magnesium is a function of pH; it rapidly degrades in acidic media, but it has acceptable stability under alkaline conditions. At pH 6.8 (buffer), the half-life of the magnesium salt is about 19 hours at 25°C and about 8 hours at 37°C.

NEXIUM is supplied in delayed-release capsules and in packets for a delayed-release oral suspension. Each delayed-release capsule contains 20 mg, or 40 mg of esomeprazole (present as 22.3 mg, or 44.5 mg esomeprazole magnesium trihydrate) in the form of enteric-coated granules with the following inactive ingredients: glyceryl monostearate 40-55, hydroxypropyl cellulose, hypromellose, magnesium stearate, methacrylic acid copolymer type C, polysorbate 80, sugar spheres, talc, and triethyl citrate. The capsule shells have the following inactive ingredients: gelatin, FD&C Blue #1, FD&C Red #40, D&C Red #28, titanium dioxide, shellac, ethyl alcohol, isopropyl alcohol, n-butyl alcohol, propylene glycol, sodium hydroxide, polyvinyl pyrrolidone, and D&C Yellow #10.

Each packet of NEXIUM For Delayed-Release Oral Suspension contains 2.5 mg, 5 mg, 10 mg, 20 mg, or 40 mg of esomeprazole, in the form of the same enteric-coated granules used in NEXIUM Delayed-Release Capsules, and also inactive granules. The inactive granules are composed of the following ingredients: dextrose, xanthan gum, crospovidone, citric acid, iron oxide, and hydroxypropyl cellulose. The esomeprazole granules and inactive granules are constituted with water to form a suspension and are given by oral, nasogastric, or gastric administration.

CLINICAL PHARMACOLOGY SECTION

12.1 Mechanism of Action

Esomeprazole is a proton pump inhibitor that suppresses gastric acid secretion by specific inhibition of the H+/K+-ATPase in the gastric parietal cell. The S- and R-isomers of omeprazole are protonated and converted in the acidic compartment of the parietal cell forming the active inhibitor, the achiral sulphenamide. By acting specifically on the proton pump, esomeprazole blocks the final step in acid production, thus reducing gastric acidity. This effect is dose-related up to a daily dose of 20 to 40 mg and leads to inhibition of gastric acid secretion.

12.2 Pharmacodynamics

Antisecretory Activity

The effect of NEXIUM on intragastric pH was determined in patients with symptomatic gastroesophageal reflux disease in two separate studies. In the first study of 36 patients, NEXIUM 40 mg and 20 mg capsules were administered over 5 days. The results are shown in the Table 3:

Table 3: Effect on Intragastric pH on Day 5 (N=36)
Parameter | NEXIUM; 40 mg | NEXIUM; 20 mg
% Time Gastric pH >4 *(Hours) | 70% †; (16.8 h) | 53%; (12.7 h)
Coefficient of variation | 26% | 37%
Median 24 Hour pH | 4.9 † | 4.1
Coefficient of variation | 16% | 27%
*Gastric pH was measured over a 24-hour period †p< 0.01 NEXIUM 40 mg vs. NEXIUM 20 mg

In a second study, the effect on intragastric pH of NEXIUM 40 mg administered once daily over a five day period was similar to the first study, (% time with pH > 4 was 68% or 16.3 hours).

Serum Gastrin Effects

The effect of NEXIUM on serum gastrin concentrations was evaluated in approximately 2,700 patients in clinical trials up to 8 weeks and in over 1,300 patients for up to 6 to 12 months. The mean fasting gastrin level increased in a dose-related manner. This increase reached a plateau within two to three months of therapy and returned to baseline levels within four weeks after discontinuation of therapy.

Increased gastrin causes enterochromaffin-like cell hyperplasia and increased serum Chromogranin A (CgA) levels. The increased CgA levels may cause false positive results in diagnostic investigations for neuroendocrine tumors. Healthcare providers should temporarily stop esomeprazole treatment at least 14 days before assessing CgA levels and consider repeating the test if initial CgA levels are high.

Enterochromaffin-like (ECL) Cell Effects

In 24-month carcinogenicity studies of omeprazole in rats, a dose-related significant occurrence of gastric ECL cell carcinoid tumors and ECL cell hyperplasia was observed in both male and female animals [see Nonclinical Toxicology (13.1)]. Carcinoid tumors have also been observed in rats subjected to fundectomy or long-term treatment with other proton pump inhibitors or high doses of H2-receptor antagonists.

Human gastric biopsy specimens have been obtained from more than 3,000 patients (both children and adults) treated with omeprazole in long-term clinical trials. The incidence of ECL cell hyperplasia in these studies increased with time; however, no case of ECL cell carcinoids, dysplasia, or neoplasia has been found in these patients.

In over 1,000 patients treated with NEXIUM (10, 20 or 40 mg/day) up to 6 to 12 months, the prevalence of ECL cell hyperplasia increased with time and dose. No patient developed ECL cell carcinoids, dysplasia, or neoplasia in the gastric mucosa.

Endocrine Effects

NEXIUM had no effect on thyroid function when given in oral doses of 20 or 40 mg for 4 weeks. Other effects of NEXIUM on the endocrine system were assessed using omeprazole studies. Omeprazole given in oral doses of 30 or 40 mg for 2 to 4 weeks had no effect on carbohydrate metabolism, circulating levels of parathyroid hormone, cortisol, estradiol, testosterone, prolactin, cholecystokinin, or secretin.

12.3 Pharmacokinetics

Absorption

NEXIUM Delayed-Release Capsules and NEXIUM For Delayed-Release Oral Suspension contain a bioequivalent enteric-coated granule formulation of esomeprazole magnesium. Bioequivalency is based on a single dose (40 mg) study in 94 healthy male and female volunteers under fasting condition. After oral administration peak plasma levels (Cmax) occur at approximately 1.5 hours (Tmax). The Cmax increases proportionally when the dose is increased, and there is a three-fold increase in the area under the plasma concentration-time curve (AUC) from 20 to 40 mg. At repeated once-daily dosing with 40 mg, the systemic bioavailability is approximately 90% compared to 64% after a single dose of 40 mg. The mean exposure (AUC) to esomeprazole increases from 4.32 µmol*hr/L on Day 1 to 11.2 µmol*hr/L on Day 5 after 40 mg once daily dosing.

The AUC after administration of a single 40 mg dose of NEXIUM is decreased by 43% to 53% after food intake compared to fasting conditions. NEXIUM should be taken at least one hour before meals.

The pharmacokinetic profile of NEXIUM was determined in 36 patients with symptomatic gastroesophageal reflux disease following repeated once daily administration of 20 mg and 40 mg capsules of NEXIUM over a period of five days. The results are shown in the Table 4:

Table 4: Pharmacokinetic Parameters of NEXIUM on Day 5 Following Oral Dosing for 5 Days
Parameter * (CV) | NEXIUM; 40 mg | NEXIUM; 20 mg
AUC (μmol·h/L) | 12.6 (42%) | 4.2 (59%)
Cmax (μmol/L) | 4.7 (37%) | 2.1 (45%)
Tmax (h) | 1.6 | 1.6
t1/2 (h) | 1.5 | 1.2
*Values represent the geometric mean, except the Tmax, which is the arithmetic mean; CV = Coefficient of variation

Distribution

Esomeprazole is 97% bound to plasma proteins. Plasma protein binding is constant over the concentration range of 2 to 20 μmol/L. The apparent volume of distribution at steady state in healthy volunteers is approximately 16 L.

Metabolism

Esomeprazole is extensively metabolized in the liver by the cytochrome P450 (CYP) enzyme system. The metabolites of esomeprazole lack antisecretory activity. The major part of esomeprazole’s metabolism is dependent upon the CYP2C19 isoenzyme, which forms the hydroxy and desmethyl metabolites. The remaining amount is dependent on CYP3A4 which forms the sulphone metabolite. CYP2C19 isoenzyme exhibits polymorphism in the metabolism of esomeprazole, since some 3% of Caucasians and 15 to 20% of Asians lack CYP2C19 and are termed Poor Metabolizers. At steady state, the ratio of AUC in Poor Metabolizers to AUC in the rest of the population (Extensive Metabolizers) is approximately 2.

Following administration of equimolar doses, the S- and R-isomers are metabolized differently by the liver, resulting in higher plasma levels of the S- than of the R-isomer.

Excretion

The plasma elimination half-life of esomeprazole is approximately 1 to 1.5 hours. Less than 1% of parent drug is excreted in the urine. Approximately 80% of an oral dose of esomeprazole is excreted as inactive metabolites in the urine, and the remainder is found as inactive metabolites in the feces.

Pharmacokinetics: Combination Therapy with Antimicrobials

Esomeprazole magnesium 40 mg once daily was given in combination with clarithromycin 500 mg twice daily and amoxicillin 1000 mg twice daily for 7 days to 17 healthy male and female subjects. The mean steady state AUC and Cmax of esomeprazole increased by 70% and 18%, respectively during triple combination therapy compared to treatment with esomeprazole alone. The observed increase in esomeprazole exposure during co-administration with clarithromycin and amoxicillin is not expected to produce significant safety concerns.

The pharmacokinetic parameters for clarithromycin and amoxicillin were similar during triple combination therapy and administration of each drug alone. However, the mean AUC and Cmax for 14-hydroxyclarithromycin increased by 19% and 22%, respectively, during triple combination therapy compared to treatment with clarithromycin alone. This increase in exposure to 14-hydroxyclarithromycin is not considered to be clinically significant.

Concomitant Use with Clopidogrel

Results from a crossover study in healthy subjects have shown a pharmacokinetic interaction between clopidogrel (300 mg loading dose/75 mg daily maintenance dose) and esomeprazole (40 mg p.o. once daily) when co-administered for 30 days. Exposure to the active metabolite of clopidogrel was reduced by 35% to 40% over this time period. Pharmacodynamic parameters were also measured and demonstrated that the change in inhibition of platelet aggregation was related to the change in the exposure to clopidogrel active metabolite.

Special Populations

Geriatric

The AUC and Cmax values were slightly higher (25% and 18%, respectively) in the elderly as compared to younger subjects at steady state. Dosage adjustment based on age is not necessary.

Pediatric (1 to 11 month of age)

The pharmacokinetic parameters following repeated dose administration of 1.0 mg/kg esomeprazole in 1 to 11 month old infants are summarized in Table 5.

Table 5: Summary of PK parameters in 1 month to < 1 year Olds with GERD Following 7/8 Days of Once-Daily Oral Esomeprazole Treatment
 | 1 month to < 1 year
Parameter | 1.0 mg/kg
AUC (μmol·h/L) (n=7) * | 3.51
Css,,max (μmol/L) (n=15) * | 0.87
t½ (hours) (n=8) * | 0.93
tmax (hours) (n=15) † | 3.0
*Geometric mean †Median

Subsequent pharmacokinetic simulation analyses showed that a dosage regimen of 2.5 mg once-daily for pediatric patients with body weight 3-5 kg, 5.0 mg once-daily for >5 to 7.5 kg and 10 mg once-daily for >7.5 to 12 kg would achieve comparable steady-state plasma exposures (AUC) to that observed after 10 mg in 1 to 11 year olds, and 20 mg in 12 to 18 year-olds as well as adults.

1 to 11 Years of Age

The pharmacokinetics of esomeprazole were studied in pediatric patients with GERD aged 1 to 11 years. Following once daily dosing for 5 days, the total exposure (AUC) for the 10 mg dose in patients aged 6 to 11 years was similar to that seen with the 20 mg dose in adults and adolescents aged 12 to 17 years. The total exposure for the 10 mg dose in patients aged 1 to 5 years was approximately 30% higher than the 10 mg dose in patients aged 6 to 11 years. The total exposure for the 20 mg dose in patients aged 6 to 11 years was higher than that observed with the 20 mg dose in 12 to 17 year-olds and adults, but lower than that observed with the 40 mg dose in 12 to 17 year-olds and adults. See Table 6.

Table 6: Summary of PK Parameters in 1 to 11 Year Olds with GERD following 5 Days of Once-Daily Oral Esomeprazole Treatment
 | 1 to 5 Year Olds | 6 to 11 Year Olds
Parameter | 10 mg (N=8) | 10 mg (N=7) | 20 mg (N=6)
AUC (μmol·h/L) * | 4.83 | 3.70 | 6.28
Cmax (μmol/L) * | 2.98 | 1.77 | 3.73
tmax (h) † | 1.44 | 1.79 | 1.75
t½λz (h) * | 0.74 | 0.88 | 0.73
Cl/F (L/h) * | 5.99 | 7.84 | 9.22
*Geometric mean; †arithmetic mean

12 to 17 Years of Age

The pharmacokinetics of NEXIUM were studied in 28 adolescent patients with GERD aged 12 to 17 years inclusive, in a single center study. Patients were randomized to receive NEXIUM 20 mg or 40 mg once daily for 8 days. Mean Cmax and AUC values of esomeprazole were not affected by body weight or age; and more than dose-proportional increases in mean Cmax and AUC values were observed between the two dose groups in the study. Overall, NEXIUM pharmacokinetics in adolescent patients aged 12 to 17 years were similar to those observed in adult patients with symptomatic GERD. See Table 7.

Table 7: Comparison of PK Parameters in 12 to 17 Year Olds with GERD and Adults with Symptomatic GERD Following the Repeated Daily Oral Dose Administration of Esomeprazole *
 | 12 to 17 Year Olds (N=28) | Adults (N=36)
 | 20 mg | 40 mg | 20 mg | 40 mg
AUC (μmol·h/L) | 3.65 | 13.86 | 4.2 | 12.6
Cmax (μmol/L) | 1.45 | 5.13 | 2.1 | 4.7
tmax (h) | 2.00 | 1.75 | 1.6 | 1.6
t½λz (h) | 0.82 | 1.22 | 1.2 | 1.5
Data presented are geometric means for AUC, Cmax and t½λz, and median value for tmax.
*Duration of treatment for 12 to 17 year olds and adults were 8 days and 5 days, respectively. Data were obtained from two independent studies.

Gender

The AUC and Cmax values were slightly higher (13%) in females than in males at steady state. Dosage adjustment based on gender is not necessary.

Hepatic Insufficiency

The steady state pharmacokinetics of esomeprazole obtained after administration of 40 mg once daily to 4 patients each with mild (Child Pugh A), moderate (Child Pugh Class B), and severe (Child Pugh Class C) liver insufficiency were compared to those obtained in 36 male and female GERD patients with normal liver function. In patients with mild and moderate hepatic insufficiency, the AUCs were within the range that could be expected in patients with normal liver function. In patients with severe hepatic insufficiency the AUCs were 2 to 3 times higher than in the patients with normal liver function. No dosage adjustment is recommended for patients with mild to moderate hepatic insufficiency (Child Pugh Classes A and B). However, in patients with severe hepatic insufficiency (Child Pugh Class C) a dose of 20 mg once daily should not be exceeded [see Dosage and Administration (2)].

Renal Insufficiency

The pharmacokinetics of NEXIUM in patients with renal impairment are not expected to be altered relative to healthy volunteers as less than 1% of esomeprazole is excreted unchanged in urine.

Other pharmacokinetic observations

Co-administration of oral contraceptives, diazepam, phenytoin, or quinidine did not seem to change the pharmacokinetic profile of esomeprazole.

Studies evaluating concomitant administration of esomeprazole and either naproxen (non-selective NSAID) or rofecoxib (COX-2 selective NSAID) did not identify any clinically relevant changes in the pharmacokinetic profiles of esomeprazole or these NSAIDs.

12.4 Microbiology

NEXIUM, amoxicillin, and clarithromycin triple therapy has been shown to be active against most strains of Helicobacter pylori (H. pylori) in vitro and in clinical infections [see Indications and Usage (1) and Clinical Studies (14)].

Helicobacter pylori: Susceptibility testing of H. pylori isolates was performed for amoxicillin and clarithromycin using agar dilution methodology, and minimum inhibitory concentrations (MICs) were determined.

Pretreatment Resistance: Clarithromycin pretreatment resistance rate (MIC ≥ 1 mcg/mL) to H. pylori was 15% (66/445) at baseline in all treatment groups combined. A total of > 99% (394/395) of patients had H. pylori isolates that were considered to be susceptible (MIC ≤ 0.25 mcg/mL) to amoxicillin at baseline. One patient had a baseline H. pylori isolate with an amoxicillin MIC = 0.5 mcg/mL.

Clarithromycin Susceptibility Test Results and Clinical/Bacteriologic Outcomes: The baseline H. pylori clarithromycin susceptibility results and the H. pylori eradication results at the Day 38 visit are shown in the Table 8:

Table 8: Clarithromycin Susceptibility Test Results and Clinical/Bacteriological Outcomes * for Triple Therapy - (Esomeprazole magnesium 40 mg once daily/amoxicillin 1000 mg twice daily/clarithromycin 500 mg twice daily for 10 days)
Clarithromycin Pretreatment Results | H. pylori negative (Eradicated) | H. pylori positive; (Not Eradicated); Post-treatment susceptibility results
 |  |  | S † | I † | R † | No MIC
Susceptible † 182 | 162 |  | 4 | 0 | 2 | 14
Intermediate † 1 | 1 |  | 0 | 0 | 0 | 0
Resistant † 29 | 13 |  | 1 | 0 | 13 | 2
*Includes only patients with pretreatment and post-treatment clarithromycin susceptibility test results †Susceptible (S) MIC ≤ 0.25 mcg/mL, Intermediate (I) MIC = 0.5 mcg/mL, Resistant (R) MIC ≥ 1.0 mcg/mL

Patients not eradicated of H. pylori following NEXIUM/amoxicillin/clarithromycin triple therapy will likely have clarithromycin resistant H. pylori isolates. Therefore, clarithromycin susceptibility testing should be done, when possible. Patients with clarithromycin resistant H. pylori should not be re-treated with a clarithromycin-containing regimen.

Amoxicillin Susceptibility Test Results and Clinical/Bacteriological Outcomes:

In the NEXIUM/amoxicillin/clarithromycin clinical trials, 83% (176/212) of the patients in the NEXIUM/amoxicillin/clarithromycin treatment group who had pretreatment amoxicillin susceptible MICs (≤ 0.25 mcg/mL) were eradicated of H. pylori, and 17% (36/212) were not eradicated of H. pylori. Of the 36 patients who were not eradicated of H. pylori on triple therapy, 16 had no post-treatment susceptibility test results and 20 had post-treatment H. pylori isolates with amoxicillin susceptible MICs. Fifteen of the patients who were not eradicated of H. pylori on triple therapy also had post-treatment H. pylori isolates with clarithromycin resistant MICs. There were no patients with H. pylori isolates who developed treatment emergent resistance to amoxicillin.

Susceptibility Test for Helicobacter pylori: For susceptibility testing information about Helicobacter pylori, see Microbiology section in prescribing information for clarithromycin and amoxicillin.

Effects on Gastrointestinal Microbial Ecology: Decreased gastric acidity due to any means, including proton pump inhibitors, increases gastric counts of bacteria normally present in the gastrointestinal tract. Treatment with proton pump inhibitors may lead to slightly increased risk of gastrointestinal infections such as Salmonella and Campylobacter and possibly Clostridium difficile in hospitalized patients.

NONCLINICAL TOXICOLOGY SECTION

13.1 Carcinogenesis, Mutagenesis, Impairment of Fertility

The carcinogenic potential of NEXIUM was assessed using studies of omeprazole, of which esomeprazole is an enantiomer. In two 24-month oral carcinogenicity studies in rats, omeprazole at daily doses of 1.7, 3.4, 13.8, 44, and 141 mg/kg/day (about 0.35 to 28 times the human dose of 40 mg/day expressed on a body surface area basis) produced gastric ECL cell carcinoids in a dose-related manner in both male and female rats; the incidence of this effect was markedly higher in female rats, which had higher blood levels of omeprazole. Gastric carcinoids seldom occur in the untreated rat. In addition, ECL cell hyperplasia was present in all treated groups of both sexes. In one of these studies, female rats were treated with 13.8 mg omeprazole/kg/day (about 2.8 times the human dose of 40 mg/day on a body surface area basis) for 1 year, then followed for an additional year without the drug. No carcinoids were seen in these rats. An increased incidence of treatment-related ECL cell hyperplasia was observed at the end of 1 year (94% treated vs. 10% controls). By the second year the difference between treated and control rats was much smaller (46% vs. 26%) but still showed more hyperplasia in the treated group. Gastric adenocarcinoma was seen in one rat (2%). No similar tumor was seen in male or female rats treated for 2 years. For this strain of rat no similar tumor has been noted historically, but a finding involving only one tumor is difficult to interpret. A 78-week mouse carcinogenicity study of omeprazole did not show increased tumor occurrence, but the study was not conclusive.

Esomeprazole was negative in the Ames mutation test, in the in vivo rat bone marrow cell chromosome aberration test, and the in vivo mouse micronucleus test. Esomeprazole, however, was positive in the in vitro human lymphocyte chromosome aberration test. Omeprazole was positive in the in vitro human lymphocyte chromosome aberration test, the in vivo mouse bone marrow cell chromosome aberration test, and the in vivo mouse micronucleus test.

The potential effects of esomeprazole on fertility and reproductive performance were assessed using omeprazole studies. Omeprazole at oral doses up to 138 mg/kg/day in rats (about 28 times the human dose of 40 mg/day on a body surface area basis) was found to have no effect on reproductive performance of parental animals.

13.2 Animal Toxicology and/or Pharmacology

Reproduction Studies

Reproduction studies have been performed in rats at oral doses up to 280 mg/kg/day (about 57 times an oral human dose of 40 mg on a body surface area basis) and in rabbits at oral doses up to 86 mg/kg/day (about 35 times an oral human dose of 40 mg on a body surface area basis) and have revealed no evidence of impaired fertility or harm to the fetus due to esomeprazole [see Pregnancy, Animal Data (8.1)].

Juvenile Animal Study

A 28-day toxicity study with a 14-day recovery phase was conducted in juvenile rats with esomeprazole magnesium at doses of 70 to 280 mg /kg/day (about 17 to 57 times a daily oral human dose of 40 mg on a body surface area basis). An increase in the number of deaths at the high dose of 280 mg/kg/day was observed when juvenile rats were administered esomeprazole magnesium from postnatal day 7 through postnatal day 35. In addition, doses equal to or greater than 140 mg/kg/day (about 34 times a daily oral human dose of 40 mg on a body surface area basis), produced treatment-related decreases in body weight (approximately 14%) and body weight gain, decreases in femur weight and femur length, and affected overall growth. Comparable findings described above have also been observed in this study with another esomeprazole salt, esomeprazole strontium, at equimolar doses of esomeprazole.

HOW SUPPLIED SECTION

NEXIUM Delayed-Release Capsules, 20 mg, are opaque, hard gelatin, amethyst colored capsules with two radial bars in yellow on the cap and NEXIUM 20 mg in yellow on the body. They are supplied as follows:

NDC 0186-5020-31 unit of use bottles of 30

NDC 0186-5022-28 unit dose packages of 100

NDC 0186-5020-54 bottles of 90

NDC 0186-5020-82 bottles of 1000

NEXIUM Delayed-Release Capsules, 40 mg, are opaque, hard gelatin, amethyst colored capsules with three radial bars in yellow on the cap and NEXIUM 40 mg in yellow on the body. They are supplied as follows:

NDC 0186-5040-31 unit of use bottles of 30

NDC 0186-5042-28 unit dose packages of 100

NDC 0186-5040-54 bottles of 90

NDC 0186-5040-82 bottles of 1000

NDC 0186-5040-35 unit of use bottles of 30

NDC 0186-5042-25 unit dose packages of 100

NDC 0186-5040-55 bottles of 90

NDC 0186-5040-85 bottles of 1000

NEXIUM For Delayed-Release Oral Suspension is supplied as a unit dose packet containing a fine yellow powder, consisting of white to pale brownish esomeprazole granules and pale yellow inactive granules. NEXIUM unit dose packets are supplied as follows:

NDC 0186-4025-01 unit dose packages of 30: 2.5 mg packets

NDC 0186-4050-01 unit dose packages of 30: 5 mg packets

NDC 0186-4010–01 unit dose packages of 30: 10 mg packets

NDC 0186-4020–01 unit dose packages of 30: 20 mg packets

NDC 0186-4040–01 unit dose packages of 30: 40 mg packets

Store at 25°C (77°F); excursions permitted to 15 to 30°C (59 to 86°F). [See USP Controlled Room Temperature]. Keep NEXIUM Delayed-Release Capsules container tightly closed. Dispense in a tight container if the NEXIUM Delayed-Release Capsules product package is subdivided.

INFORMATION FOR PATIENTS SECTION

“See FDA-Approved Medication Guide”

•Advise patients to let you know if they are taking, or begin taking, other medications, because NEXIUM can interfere with antiretroviral drugs and drugs that are affected by gastric pH changes [see Drug Interactions (7.1)].•Let patients know that antacids may be used while taking NEXIUM.•Advise patients to take NEXIUM at least one hour before a meal.•For patients who are prescribed NEXIUM Delayed-Release Capsules, advise them not to chew or crush the capsules.•Advise patients that, if they open NEXIUM Delayed-Release Capsules to mix the granules with food, the granules should only be mixed with applesauce. Use with other foods has not been evaluated and is not recommended.•For patients who are advised to open the NEXIUM Delayed-Release Capsules before taking them or who are prescribed NEXIUM For Delayed-Release Oral Suspension, instruct them in the proper technique for administration [see Dosage and Administration (2)] and tell them to follow the dosing instructions in the PATIENT INFORMATION insert included in the package. Instruct patients to rinse the syringe with water after each use.•For patients who are prescribed NEXIUM for Delayed-Release Oral Suspension and need to use more than one packet for their dose, instruct them regarding the correct amount of water to use when mixing their dose.

Advise patients to immediately report and seek care for diarrhea that does not improve. This may be a sign of Clostridium difficile associated diarrhea [see Warnings and Precautions (5.3)].

Advise patients to immediately report and seek care for any cardiovascular or neurological symptoms including palpitations, dizziness, seizures, and tetany as these may be signs of hypomagnesemia [see Warnings and Precautions (5.6)].

Distributed by:

AstraZeneca LP

Wilmington, DE 19850

NEXIUM and the color purple as applied to the capsule are registered trademarks of the AstraZeneca group of companies.

©AstraZeneca 2014

Rev. 03/2014

SPL MEDGUIDE SECTION

NEXIUM® (nex-e-um)

(esomeprazole magnesium)

Delayed-Release Capsules

NEXIUM® (nex-e-um)

(esomeprazole magnesium)

For Delayed-Release

Oral Suspension

Read the Medication Guide that comes with NEXIUM before you start taking NEXIUM and each time you get a refill. There may be new information. This information does not take the place of talking with your doctor about your medical condition or your treatment.

What is the most important information I should know about NEXIUM?

NEXIUM may help your acid-related symptoms, but you could still have serious stomach problems. Talk with your doctor.

NEXIUM can cause serious side effects, including:

•Diarrhea. NEXIUM may increase your risk of getting severe diarrhea. This diarrhea may be caused by an infection (Clostridium difficile) in your intestines.

Call your doctor right away if you have watery stool, stomach pain, and fever that does not go away.•Bone fractures. People who take multiple daily doses of Proton Pump Inhibitor medicines for a long period of time (a year or longer) may have an increased risk of fractures of the hip, wrist, or spine. You should take NEXIUM exactly as prescribed, at the lowest dose possible for your treatment and for the shortest time needed. Talk to your doctor about your risk of bone fracture if you take NEXIUM.

NEXIUM can have other serious side effects. See “ What are the possible side effects of NEXIUM?”

What is NEXIUM?

NEXIUM is a prescription medicine called a proton pump inhibitor (PPI). NEXIUM reduces the amount of acid in your stomach.

NEXIUM is used in adults:

•for 4 to 8 weeks to treat the symptoms of gastroesophageal reflux disease (GERD). NEXIUM may also be prescribed to heal acid-related damage to the lining of the esophagus (erosive esophagitis), and to help continue this healing.•GERD happens when acid in your stomach backs up into the tube (esophagus) that connects your mouth to your stomach. This may cause a burning feeling in your chest or throat, sour taste, or burping.•for up to 6 months to reduce the risk of stomach ulcers in some people taking pain medicines called non-steroidal anti-inflammatory drugs (NSAIDs).•to treat patients with a stomach infection (Helicobacter pylori), along with the antibiotics amoxicillin and clarithromycin.•for the long-term treatment of conditions where your stomach makes too much acid, including Zollinger-Ellison Syndrome. Zollinger-Ellison Syndrome is a rare condition in which the stomach produces a more than normal amount of acid.

For children and adolescents 1 year to 17 years of age, NEXIUM may be prescribed for up to 8 weeks for short-term treatment of GERD.

In children ages 1 month to less than 1 year of age, NEXIUM is only used to treat GERD with acid-related damage to the esophagus (erosive esophagitis) for up to 6 weeks.

It is not known if NEXIUM is effective in children under 1 month of age.

Who should not take NEXIUM?

Do not take NEXIUM if you:

•are allergic to esomeprazole magnesium or any of the ingredients in NEXIUM. See the end of this Medication Guide for a complete list of ingredients in NEXIUM.•are allergic to any other Proton Pump Inhibitor (PPI) medicine.

What should I tell my doctor before taking NEXIUM?

Before you take NEXIUM, tell your doctor if you:

•have been told that you have low magnesium levels in your blood•have liver problems•are pregnant or plan to become pregnant. It is not known if NEXIUM can harm your unborn baby.•are breastfeeding or planning to breastfeed. NEXIUM may pass into your breast milk. Talk to your doctor about the best way to feed your baby if you take NEXIUM.

Tell your doctor about all of the medicines you take, including prescription and non-prescription drugs, vitamins and herbal supplements. NEXIUM may affect how other medicines work, and other medicines may affect how NEXIUM works.

•Especially tell your doctor if you take:•warfarin (Coumadin, Jantoven)•ketoconazole (Nizoral)•voriconazole (Vfend)•atazanavir (Reyataz)•nelfinavir (Viracept)•saquinavir (Fortovase)•products that contain iron•digoxin (Lanoxin)•St.John’s Wort (Hypericum perforatum)•Rifampin (Rimactane, Rifater, Rifamate)•cilostazol (Pletal)•diazepam (Valium)•tacrolimus (Prograf)•erlotinib (Tarceva)•methotrexate•clopidogrel (Plavix)

How should I take NEXIUM?

•Take NEXIUM exactly as prescribed by your doctor.•Do not change your dose or stop NEXIUM without talking to your doctor.•Take NEXIUM at least 1 hour before a meal.•Swallow NEXIUM capsules whole. Never chew or crush NEXIUM.•If you have difficulty swallowing NEXIUM capsules, you may open the capsule and empty the contents into a tablespoon of applesauce. Do not crush or chew the granules. Be sure to swallow the applesauce right away. Do not store it for later use.•If you forget to take a dose of NEXIUM, take it as soon as you remember. If it is almost time for your next dose, do not take the missed dose. Take the next dose on time. Do not take a double dose to make up for a missed dose.•If you take too much NEXIUM, call your doctor or local poison control center right away, or go to the nearest hospital emergency room.•See the “Instructions for Use” at the end of this Medication Guide for instructions how to take NEXIUM For Delayed-Release Oral Suspension, and how to mix and give NEXIUM Delayed-Release Capsules and NEXIUM For Delayed-Release Oral Suspension, through a nasogastric tube or gastric tube.

What are the possible side effects of NEXIUM?

NEXIUM can cause serious side effects, including:

•See “ What is the most important information I should know about NEXIUM?”•Chronic (lasting a long time) inflammation of the stomach lining (Atrophic Gastritis). Using NEXIUM for a long period of time may increase the risk of inflammation to your stomach lining. You may or may not have symptoms. Tell your doctor if you have stomach pain, nausea, vomiting, or weight loss.•Low magnesium levels in your body. Low magnesium can happen in some people who take a proton pump inhibitor medicine for at least 3 months. If low magnesium levels happen, it is usually after a year of treatment.

You may or may not have symptoms of low magnesium. Tell your doctor right away if you have any of these symptoms:

∘seizures∘dizziness∘abnormal or fast heart beat∘jitteriness∘jerking movements or shaking (tremors)∘muscle weakness∘spasms of the hands and feet∘cramps or muscle aches∘spasm of the voice box

Your doctor may check the level of magnesium in your body before you start taking NEXIUM or during treatment if you will be taking NEXIUM for a long period of time.

The most common side effects with NEXIUM may include:

∘headache∘diarrhea∘nausea∘gas∘abdominal pain∘constipation∘dry mouth∘drowsiness

Other side effects:

Serious allergic reactions. Tell your doctor if you get any of the following symptoms with NEXIUM:

•rash•face swelling•throat tightness•difficulty breathing

Your doctor may stop NEXIUM if these symptoms happen.

Tell your doctor if you have any side effects that bother you or that do not go away. These are not all the possible side effects with NEXIUM.

Call your doctor for medical advice about side effects. You may report side effects to FDA at 1-800-FDA-1088.

How should I store NEXIUM?

•Store NEXIUM at room temperature between 68°F to 77°F (20°C to 25°C).•Keep the container of NEXIUM closed tightly.

Keep NEXIUM and all medicines out of the reach of children.

General information about NEXIUM

Medicines are sometimes prescribed for purposes other than those listed in a Medication Guide. Do not use NEXIUM for a condition for which it was not prescribed. Do not give NEXIUM to other people, even if they have the same symptoms you have. It may harm them.

This Medication Guide summarizes the most important information about NEXIUM. If you would like more information, talk with your doctor. You can ask your pharmacist or doctor for information about NEXIUM that is written for health professionals.

For more information, go to www.purplepill.com or call 1-800-463-9486.

What are the ingredients in NEXIUM?

Active ingredient: esomeprazole magnesium trihydrate

Inactive ingredients in NEXIUM Delayed-Release Capsules (including the capsule shells): glyceryl monostearate 40-55, hydroxypropyl cellulose, hypromellose, magnesium stearate, methacrylic acid copolymer type C, polysorbate 80, sugar spheres, talc, triethyl citrate, gelatin, FD&C Blue #1, FD&C Red #40, D&C Red #28, titanium dioxide, shellac, ethyl alcohol, isopropyl alcohol, n-butyl alcohol, propylene glycol, sodium hydroxide, polyvinyl pyrrolidone, and D&C Yellow #10.

Inactive granules in NEXIUM For Delayed-Release Oral Suspension: dextrose, xanthan gum, crospovidone, citric acid, iron oxide, and hydroxypropyl cellulose.

Instructions for Use

For instructions on taking Delayed-Release Capsules, see the section of this leaflet called “How should I take NEXIUM?”

Take NEXIUM For Delayed-Release Oral Suspension as follows:

•NEXIUM For Delayed-Release Oral Suspension comes in foil packets containing 2.5 mg, 5 mg, 10 mg, 20 mg, or 40 mg strengths.•You should use an oral syringe to measure the amount of water needed to mix your dose. Ask your pharmacist for an oral syringe.•If your prescribed dose is 2.5 mg or 5 mg, add 5 mL of water to a container, then add the contents of a foil packet containing the dose prescribed by your doctor.•If your prescribed dose is 10 mg, 20 mg, or 40 mg, add 15 mL of water to a container, then add the contents of a foil packet containing the dose prescribed by your doctor.•If you or your child are instructed to use more than one foil packet for the prescribed dose, follow the mixing instructions provided by your pharmacist or doctor.•Stir.•Leave 2 to 3 minutes to thicken.•Stir and take dose within 30 minutes. If not used within 30 minutes, throw away this dose and mix a new dose.•If any medicine remains after drinking, add more water, stir, and take dose right away.•For young children, you can give the dose with an oral syringe. Rinse the oral syringe with water after each use.

NEXIUM Delayed-Release Capsules and NEXIUM For Delayed-Release Oral Suspension may be given through a nasogastric tube (NG tube) or gastric tube, as prescribed by your doctor. Follow the instructions below:

NEXIUM Delayed-Release Capsules:

•Open the capsule and empty the granules into a 60 mL catheter tipped syringe. Mix with 50 mL of water. Use only a catheter tipped syringe to give NEXIUM through a NG tube.•Replace the plunger and shake the syringe well for 15 seconds. Hold the syringe with the tip up and check for granules in the tip.•Give the medicine right away.•Do not give the granules if they have dissolved or have broken into pieces.•Attach the syringe to the NG tube. Give the medicine in the syringe through the NG tube into the stomach.•After giving the granules, flush the NG tube with more water.

NEXIUM For Delayed-Release Oral Suspension:

•NEXIUM For Delayed-Release Oral Suspension comes in foil packets containing 2.5 mg, 5 mg, 10 mg, 20 mg, or 40 mg strengths.•Use only a catheter tipped syringe to give NEXIUM through a NG tube or gastric tube•If your prescribed dose is 2.5 mg or 5 mg, add 5 mL of water to a catheter tipped syringe, then add the contents of a foil packet containing the dose prescribed by your doctor.•If your prescribed dose is 10 mg, 20 mg, or 40 mg, add 15 mL of water to a catheter tipped syringe, then add the contents of a foil packet containing the dose prescribed by your doctor.•Shake the syringe right away and then leave it for 2 to 3 minutes to thicken.•Shake the syringe and give the medicine through the NG or gastric tube (French size 6 or larger) into the stomach within 30 minutes.•Refill the syringe with the same amount of water (either 5 mL or 15 mL of water depending on your dose).•Shake the syringe and flush any remaining medicine from the NG tube or gastric tube into the stomach.

This Medication Guide has been approved by the U.S. Food and Drug Administration.

AstraZeneca Pharmaceuticals LP

Wilmington, DE 19850

Revised March 2014

NEXIUM is a registered trademark of the AstraZeneca group of companies.

©2014 AstraZeneca Pharmaceuticals LP. All rights reserved